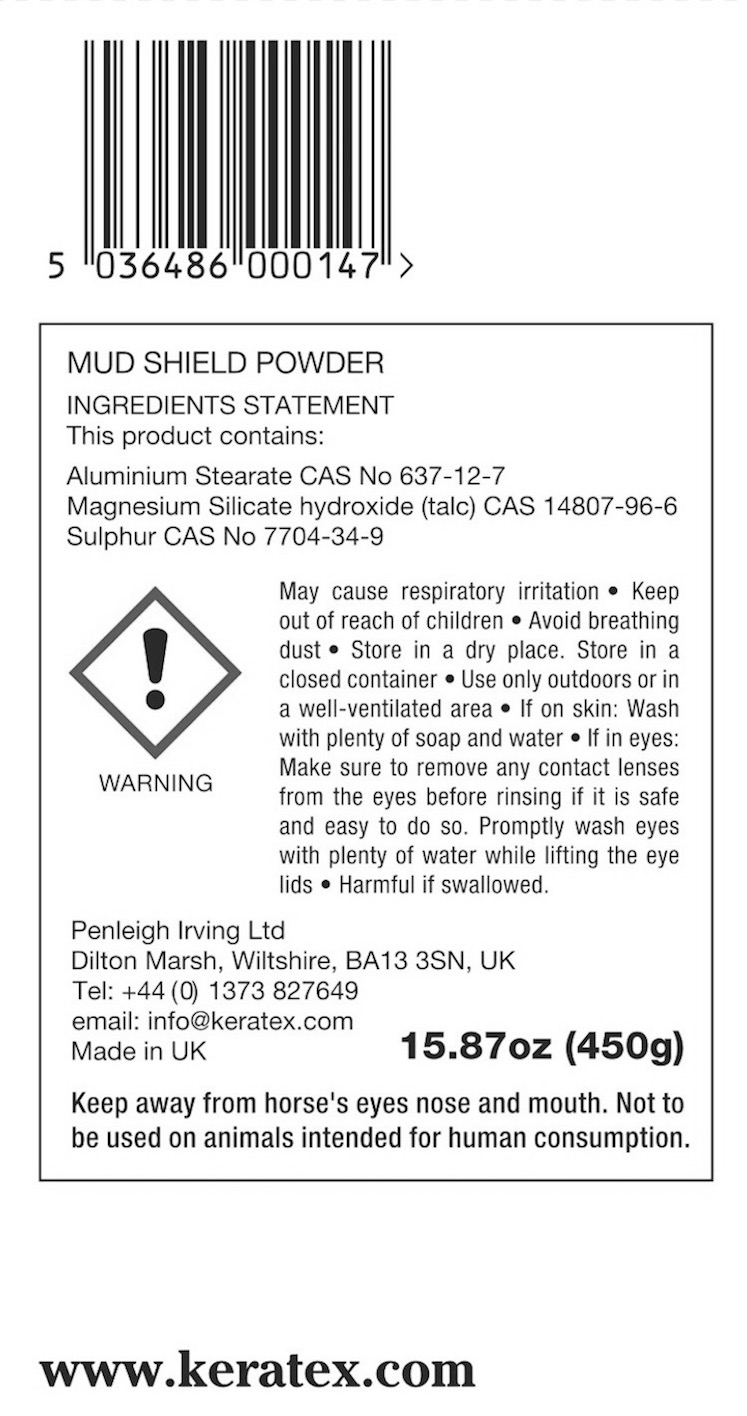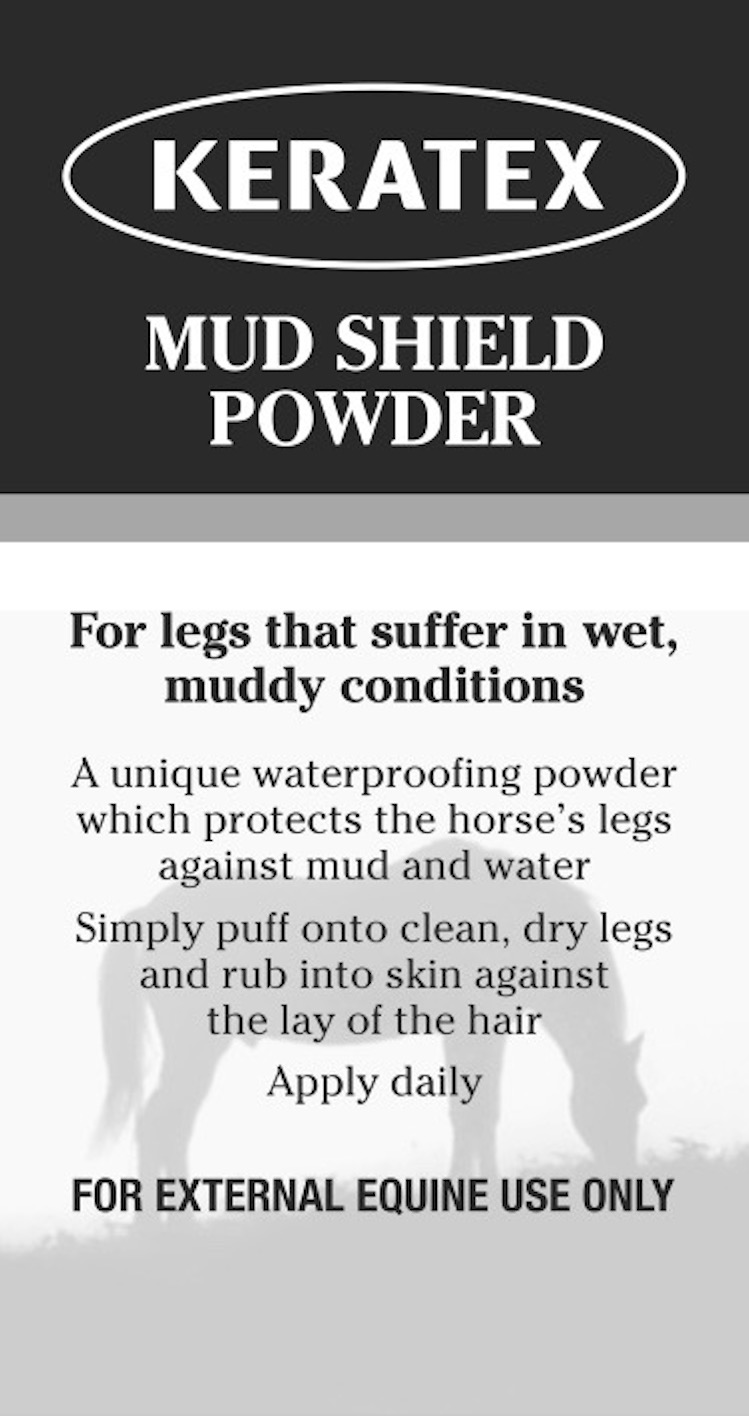 DRUG LABEL: Keratex
NDC: 27426-060 | Form: POWDER
Manufacturer: Penleigh Irving Ltd
Category: animal | Type: OTC ANIMAL DRUG LABEL
Date: 20180815

ACTIVE INGREDIENTS: ALUMINUM STEARATE 0.05 g/2 g; SULFUR .093 g/2 g

SAFE HANDLING WARNING

May cause respiratory irritation. Keep out of reach of children. Avoid breathing dust. Store in a dry place. Store in a closed container. Use only outdoors or in a well-ventilated area. If on skin: Wash with plenty of soap and water. If in eyes: Make sure to remove any contact lenses from the eyes before rinsing if it is safe and easy to do. Promptly wash eyes and with plenty of water while lifting the eye lids. Harmful if swallowed.

PACKAGE LABEL

Keratex Mud Shield Powder

For legs that suffer in wet, muddy conditions

A unique waterproofing powder which protects the horse's legs against mud and water. Simply puff onto clean, dry legs and rub into skin against the lay of the hair. Apply daily.

For External Equine Use Only

Ingredients Statement. This product contains: Aluminium Stearate CAS No. 637-12-7

Magnesium Silicate hydroxide (talc) CAS 14807-96-6

Sulphur CAS No. 7704-34-9

Keep away from horse’s eyes, nose and mouth. Not to be used on animals intended for human consumption.

Penleigh Irving Ltd

Dilton Marsh, Wiltshire, BK13 3SN, UK

+44 (0) 1373 827649 email: info@keratex.com

Made in UK 15.87 oz (450g)

www.keratex.com